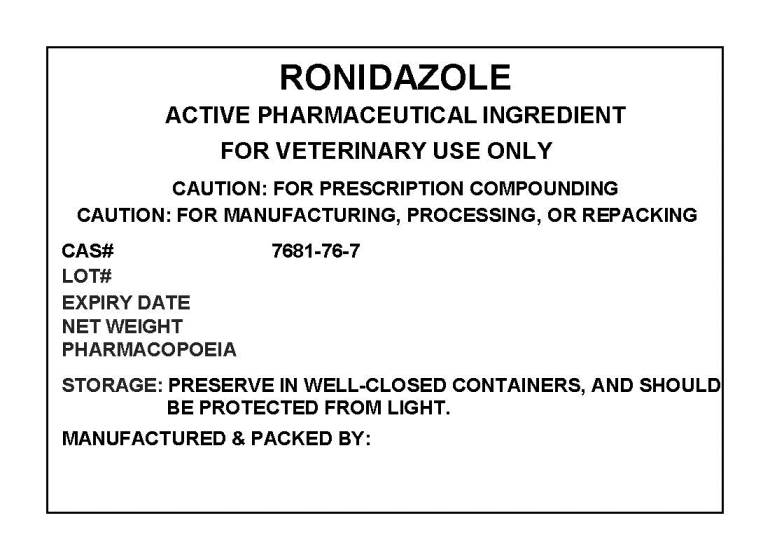 DRUG LABEL: RONIDAZOLE
NDC: 72969-065 | Form: POWDER
Manufacturer: PROFESSIONAL GROUP OF PHARMACISTS NEW YORK LLC
Category: other | Type: BULK INGREDIENT
Date: 20190314

ACTIVE INGREDIENTS: RONIDAZOLE 1 g/1 g

RONIDAZOLE

PACKAGE LABEL

ronidazolelabel.jpg